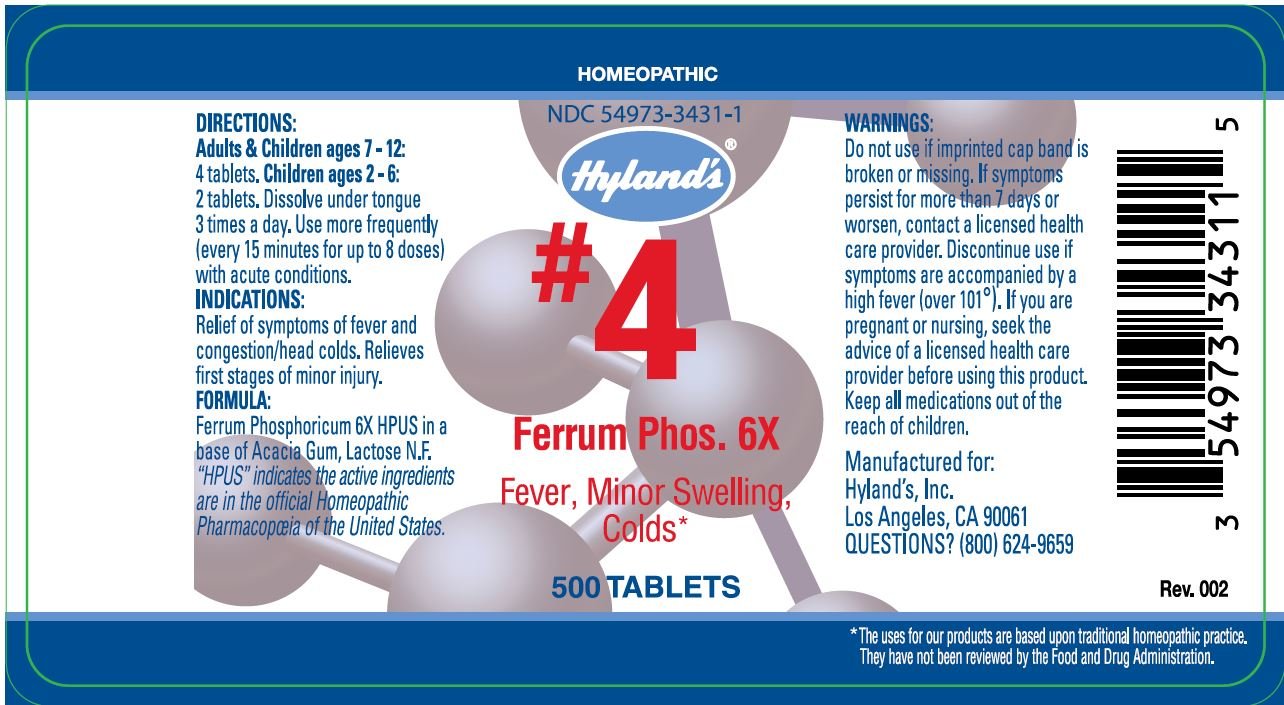 DRUG LABEL: FERRUM PHOSPHATE
NDC: 54973-3431 | Form: TABLET
Manufacturer: Hyland's Inc.
Category: homeopathic | Type: HUMAN OTC DRUG LABEL
Date: 20221219

ACTIVE INGREDIENTS: SODIUM PHOSPHATE 6 [hp_X]/1 1
INACTIVE INGREDIENTS: ACACIA; LACTOSE

FERRUM PHOSPHATE

DIRECTIONS

Adults & Children ages 6 - 12: 4 tablets. Children ages 2 - 6: 2 tablets. Dissolve under tongue 3 times a day. Use more frequently (every 15 minutes for up to 8 doses) with acute conditions.

INDICATIONS

Relief of symptoms of fevers and congestion/head colds. Relieves the first stages of minor injury.

PURPOSE

Fever, Minor Swelling, Colds

FORMULA

Ferrum Phosphoricum 6X HPUS

INACTIVE INGREDIENT

in a base of Acacia Gum, Lactose N.F.

“HPUS” indicates that the active ingredients are in the official Homeopathic Pharmacopœia of the United States.

Warnings

Do not use if imprinted cap band is broken or missing.

ASK DOCTOR

If symptoms persist for more than 7 days or worsen, contact a licensed health care provider.

STOP USE

Discontinue use if symptoms are accompanied by a high fever (over 101°F).

PREGNANCY OR BREAST FEEDING

If you are pregnant or nursing, seek the advice of a licensed health care provider before using this product.

KEEP OUT OF REACH OF CHILDREN

Keep all medications out of the reach of children.

QUESTIONS?

(800) 624-9659

PRINCIPAL DISPLAY PANEL - 500 Tablet Bottle Label

HOMEOPATHIC

NDC 54973-3431-1

Hyland's®

#4

Ferrum Phos. 6X

Fevers,Minor Swelling,
Colds

500 TABLETS